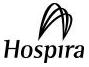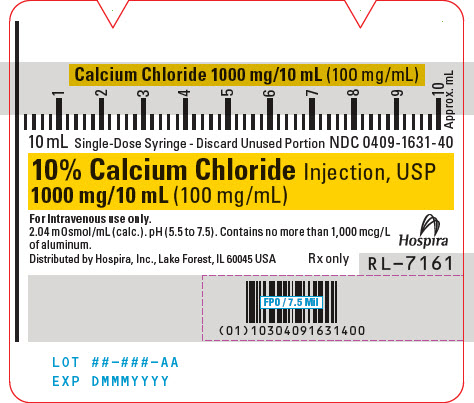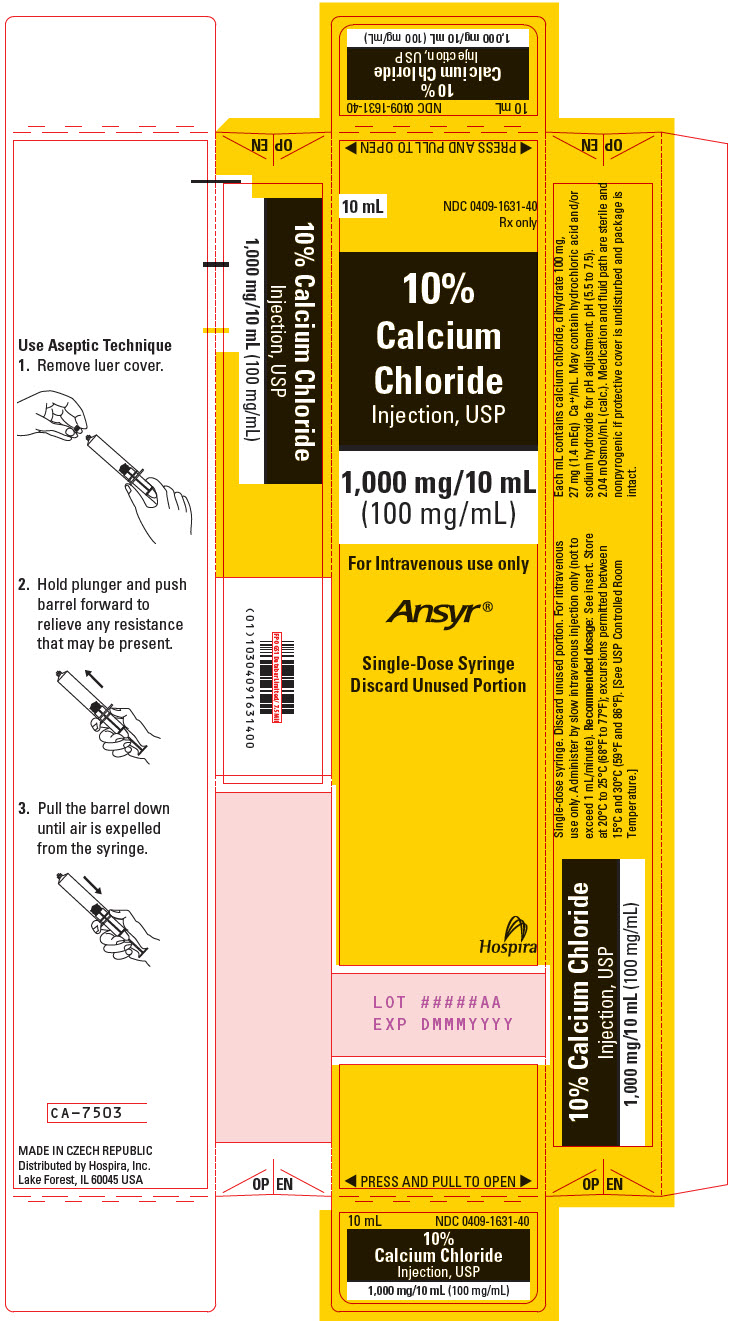 DRUG LABEL: Calcium Chloride
NDC: 0409-1631 | Form: INJECTION, SOLUTION
Manufacturer: Hospira, Inc.
Category: prescription | Type: HUMAN PRESCRIPTION DRUG LABEL
Date: 20260202

ACTIVE INGREDIENTS: CALCIUM CHLORIDE 100 mg/1 mL
INACTIVE INGREDIENTS: WATER; HYDROCHLORIC ACID; SODIUM HYDROXIDE

HIGHLIGHTS OF PRESCRIBING INFORMATION

These highlights do not include all the information needed to use 10% CALCIUM CHLORIDE INJECTION safely and effectively. See full prescribing information for 10% CALCIUM CHLORIDE INJECTION.
CALCIUM CHLORIDE injection, for intravenous use only
Initial U.S. Approval: 1938

1 INDICATIONS AND USAGE

Calcium Chloride Injection is a form of calcium indicated for the treatment of adult and pediatric and patients with acute symptomatic hypocalcemia. (1)

Limitations of Use:

The safety and effectiveness of Calcium Chloride Injection for long-term use has not been established.

2 DOSAGE AND ADMINISTRATION

- Administer Calcium Chloride Injection by slow intravenous infusion (not to exceed 1 mL/minute), in a central or deep vein. (2.1)
- Do not use intramuscularly or subcutaneously. (2.1)
- Do not administer unless solution is clear and seal is intact. (2.1)
- Stop the administration if the patient complains of any administration-related discomfort, it may be resumed when symptoms disappear. (2.1)
- The recommended adult dose is from 200 mg to 1,000 mg. (2.2)
- The recommended pediatric dose is from 2.7 to 5 mg/kg of calcium chloride. (2.2)
- Repeated injections may be required because of rapid calcium excretion. (2.2)
- See the full prescribing information for the recommended starting dose in patients with renal impairment. (2.3)
- Do not mix Calcium Chloride Injection with ceftriaxone or administer these products simultaneously via a Y-site because concurrent use can lead to the formation of ceftriaxone-calcium precipitates. (2.4)

3 DOSAGE FORMS AND STRENGTHS

Calcium Chloride Injection, USP (single-dose) is supplied as: (3)

- 10% (1,000 mg/10 mL) (100 mg/mL) in an Ansyr® Plastic Syringe

The 100 mg/mL concentration represents 27 mg or 1.4 mEq of elemental calcium per mL of solution. (3)

4 CONTRAINDICATIONS

Calcium Chloride Injection is contraindicated in:

- Patients with ventricular fibrillation. (4)
- Patients with asystole and electromechanical dissociation. (4)
- Newborns (up to 28 days of age) if they require (or are expected to require) ceftriaxone intravenous treatment, regardless of whether these products would be received at different times or through separate intravenous lines. (4, 5.1)

5 WARNINGS AND PRECAUTIONS

- End-Organ Damage due to Intravascular Ceftriaxone-Calcium Precipitates: Calcium Chloride Injection is contraindicated in newborns (up to 28 days of age) if they require (or are expected to require) ceftriaxone intravenous treatment. In patients older than 28 days of age, do not mix or administer simultaneously with ceftriaxone intravenous solutions, even via different infusion lines or at different infusion sites as it can lead to precipitation of ceftriaxone-calcium. (5.1)
- Hypotension, Bradycardia, Arrhythmias, and Syncope with Rapid Administration: Too rapid an injection exceeding 1 mL/minute may lead to hypotension and syncope. (2.1, 5.2)
- Arrhythmias with Concomitant Digoxin Use: Avoid use of Calcium Chloride Injection in patients receiving digoxin. Closely monitor ECG and calcium levels if concomitant therapy is necessary. (5.3, 7.1)
- Tissue Necrosis and Calcinosis: Administer Calcium Chloride Injection slowly through a small needle into a large vein to minimize the risk of tissue necrosis, ulceration and calcinosis. Avoid extravasation or accidental injection into perivascular tissues. Immediately discontinue administration should perivascular infiltration occur. (2.1, 5.4)
- Aluminum Toxicity: Risk of toxicity with prolonged administration if kidney function is impaired. Premature neonates are particularly at risk. When prescribing Calcium Chloride Injection in patients receiving parenteral nutrition solutions, limit the total daily patient exposure to aluminum to no more than 5 mcg/kg/day. (5.5)

6 ADVERSE REACTIONS

Adverse reactions have included paraesthesia (upon rapid injection), calcium taste, sense of oppression, sense of “heat wave”, local burning sensation, injection site extravasation, injection site reactions, peripheral vasodilatation, and decreased blood pressure. (6)

To report SUSPECTED ADVERSE REACTIONS, contact Pfizer Inc. at 1-800-438-1985 or FDA at 1-800-FDA-1088 or www.fda.gov/medwatch.

7 DRUG INTERACTIONS

- Digoxin: Avoid concomitant use with Calcium Chloride Injection. If concomitant use is unavoidable, monitor ECG closely during administration of Calcium Chloride Injection. (5.3, 7.1)
- Calcium Channel Blockers: Avoid concomitant use with Calcium Chloride Injection. If concomitant use is unavoidable, monitor blood pressure closely during administration of Calcium Chloride Injection. (7.2)
- Drugs That Increase the Risk of Hypercalcemia: Increase the frequency of calcium concentration monitoring in patients taking Calcium Chloride Injection concomitantly with other drugs that increase the risk of hypercalcemia. (7.3)

FULL PRESCRIBING INFORMATION

1 INDICATIONS AND USAGE

Calcium Chloride Injection is indicated for the treatment of adult and pediatric patients with acute symptomatic hypocalcemia.

Limitations of Use

The safety and effectiveness of Calcium Chloride Injection for long-term use has not been established.

2 DOSAGE AND ADMINISTRATION

2.1 Important Administration Instructions

Administer Calcium Chloride Injection by slow intravenous infusion in a central or deep vein in adults and pediatric patients (with or without renal impairment); do not administer by bolus [see Warnings and Precautions (5.2, 5.4)]. The maximum recommended infusion rate is 1 mL/minute (100 mg/minute).

Additional important administration instructions regarding Calcium Chloride Injection are as follows:

- Do not use intramuscularly or subcutaneously to avoid tissue necrosis calcinosis cutis [see Warnings and Precautions (5.4)].
- Visually inspect for particulate matter and discoloration prior to administration (the solution is clear, and the seal is intact). Do not administer if the solution is unclear or the seal is not intact.
- Stop the administration if the patient complains of any administration-related discomfort; administration may be resumed when symptoms disappear.
- Discard the unused portion.
- If time permits, allow the solution to warm to body temperature.

2.2 Recommended Dosage and Administration

The recommended dose range of Calcium Chloride Injection in:

- Adults is from 200 mg to 1,000 mg.
- Pediatric patients is from 2.7 to 5 mg/kg of calcium chloride.

Dosing of this Calcium Chloride Injection product is not possible in patients who require doses less than 200 mg because the recommended dose cannot be achieved with the supplied syringe. For patients who require doses less than 200 mg, use another calcium chloride injection product that allows dosing of less than 200 mg.

Individualize the dose for a patient within these dose ranges depending on serum ionized calcium level, severity of hypocalcemia symptoms, and the acuity of hypocalcemia onset.

Repeated injections may be required because of rapid excretion of calcium.

2.3 Recommended Starting Dose in Patients with Renal Impairment

The recommended starting dose of Calcium Chloride Injection in [see Use in Specific Populations (8.6)]:

- Adults with renal impairment is 200 mg.
- Pediatric patients is 2.7 mg/kg of calcium chloride.

2.4 Drug Incompatibilities

Do not mix Calcium Chloride Injection with other drugs simultaneously. Do not mix Calcium Chloride Injection with ceftriaxone or administer these products simultaneously via a Y-site because concurrent use can lead to the formation of ceftriaxone-calcium precipitates [see Warnings and Precautions (5.1)]:

- In neonates (28 days of age or younger), concomitant use of Calcium Chloride Injection and ceftriaxone is contraindicated [see Contraindications (4)].
- In patients older than 28 days of age, ceftriaxone and calcium-containing products may be administered sequentially, provided the infusion lines are thoroughly flushed between infusions with a compatible fluid.

3 DOSAGE FORMS AND STRENGTHS

Calcium Chloride Injection, USP (single-dose) supplied as:

- 10% (1,000 mg/10 mL) (100 mg/mL) in an Ansyr® Plastic Syringe

The 100 mg/mL concentration represents 27 mg or 1.4 mEq of elemental calcium per mL of solution.

4 CONTRAINDICATIONS

Calcium Chloride Injection is contraindicated in:

- Patients with ventricular fibrillation
- Patients with asystole and electromechanical dissociation

Newborns (up to 28 days of age) if they require (or are expected to require) ceftriaxone intravenous treatment because of the risk of precipitation of ceftriaxone-calcium, regardless of whether these products would be received at different times or through separate intravenous lines [see Warnings and Precautions (5.1)].

5 WARNINGS AND PRECAUTIONS

5.1 End-Organ Damage due to Intravascular Ceftriaxone-Calcium Precipitates

The use of Calcium Chloride Injection is contraindicated in newborns (up to 28 days of age) if they require (or are expected to require) ceftriaxone intravenous treatment because of the risk of precipitation of ceftriaxone-calcium, regardless of whether these products would be received at different times or through separate intravenous lines [see Contraindications (4)]. Cases of fatal reactions with calcium-ceftriaxone precipitates in lungs and kidneys in premature and full-term newborns aged less than 1 month have occurred when ceftriaxone and calcium were administered either simultaneously or non-simultaneously and through different intravenous lines. In-vitro studies demonstrated that neonates have an increased risk of precipitation of ceftriaxone-calcium compared to other age groups.

In patients older than 28 days of age, Calcium Chloride Injection and ceftriaxone intravenous solutions may be administered sequentially one after another if infusion lines at different sites are used, infusion lines are replaced, or infusion lines are thoroughly flushed between infusions with physiological salt solution to avoid precipitation. Do not mix or administer Calcium Chloride Injection simultaneously with ceftriaxone, even if using different infusion lines or different infusion sites as it can lead to precipitation of ceftriaxone-calcium [see Dosage and Administration (2.4)].

5.2 Hypotension, Bradycardia, Arrhythmias, and Syncope with Rapid Administration

Rapid injection of Calcium Chloride Injection may cause vasodilation, decreased blood pressure, bradycardia, arrhythmias, syncope, and cardiac arrest. It is particularly important to prevent a high concentration of calcium from reaching the heart because of the risk of syncope. Too rapid an injection exceeding 1 mL/minute may lead to hypotension and cardiac syncope [see Dosage and Administration (2.1)].

5.3 Arrhythmias with Concomitant Digoxin Use

Arrhythmias may occur if Calcium Chloride Injection and digoxin are administered together. Hypercalcemia resulting from an overdose of Calcium Chloride Injection increases the risk of digoxin toxicity. Avoid the use of Calcium Chloride Injection in patients receiving digoxin. If concomitant therapy is necessary, closely monitor ECG and calcium levels [see Drug Interactions (7.1)].

5.4 Tissue Necrosis and Calcinosis

Administration of Calcium Chloride Injection in patients with local trauma may result in calcinosis cutis due to transient increase in local calcium concentration. Calcinosis cutis can occur with or without extravasation of Calcium Chloride Injection, is characterized by abnormal dermal deposits of calcium salts, and clinically manifests as papules, plaques, or nodules that may be associated with erythema, swelling, or induration. Tissue necrosis, ulceration, and secondary infection are the most serious complications.

To minimize the risk of tissue necrosis, ulceration and calcinosis, administer Calcium Chloride Injection slowly through a small needle into a large vein [see Dosage and Administration (2.1)]. Avoid extravasation or accidental injection into perivascular tissues. Should perivascular infiltration occur, immediately discontinue intravenous administration at that site and treat as needed.

5.5 Aluminum Toxicity

Calcium Chloride Injection contains aluminum that may be toxic. Aluminum may reach toxic levels with prolonged parenteral administration if kidney function is impaired. Premature neonates are particularly at risk because their kidneys are immature, and they require large amounts of calcium and phosphate solutions, which contain aluminum. Research indicates that patients with impaired kidney function, including premature (preterm) neonates and preterm infants, who receive parenteral levels of aluminum at greater than 4 to 5 mcg/kg/day can accumulate aluminum at levels associated with central nervous system and bone toxicity. Tissue loading may occur at even lower amounts of aluminum.

Exposure to aluminum from Calcium Chloride Injection at the recommended dose is not more than 10 mcg [see Dosage and Administration (2.2) and Description (11)]. When prescribing Calcium Chloride Injection in patients receiving parenteral nutrition solutions, limit the total daily patient exposure to aluminum to no more than 5 mcg/kg/day.

6 ADVERSE REACTIONS

The following serious adverse reactions are also described elsewhere in the labeling:

- End-Organ Damage due to Intravascular Ceftriaxone-Calcium Precipitates [see Warnings and Precautions (5.1)]
- Hypotension, Bradycardia, Arrhythmias, and Syncope with Rapid Administration [see Warnings and Precautions (5.2)]
- Arrhythmias with Concomitant Digoxin Use [see Warnings and Precautions (5.3)]
- Tissue Necrosis and Calcinosis [see Warnings and Precautions (5.4)]
- Aluminum toxicity [see Warnings and Precautions (5.5)]

The following adverse reactions have been identified in literature and postmarketing reports of calcium chloride. Because some of these reactions were reported voluntarily from a population of uncertain size, it is not always possible to reliably estimate their frequency or establish a causal relationship to drug exposure:

- Nervous system disorders: Paraesthesia (upon rapid injection), calcium taste
- General disorders and administration site conditions: Sense of oppression, sense of “heat wave”, local burning sensation, injection site extravasation, injection site reactions
- Cardiovascular disorders: Peripheral vasodilatation, decreased blood pressure

7 DRUG INTERACTIONS

7.1 Digoxin

Avoid the concomitant use of Calcium Chloride Injection with digoxin. If concomitant use is unavoidable, monitor ECG closely during administration of Calcium Chloride Injection.

Synergistic arrhythmias may occur with concomitant use. The use of Calcium Chloride Injection may result in hypercalcemia which increases the risk of digoxin toxicity [see Warnings and Precautions (5.3)].

7.2 Calcium Channel Blockers

Concomitant use of Calcium Chloride Injection and calcium channel blockers may reduce the response to calcium channel blockers. Avoid concomitant use. If concomitant use is unavoidable, monitor blood pressure closely during administration of Calcium Chloride Injection.

7.3 Drugs That Increase the Risk of Hypercalcemia

Increase frequency of monitoring of calcium concentrations in patients taking concomitant Calcium Chloride Injection and other drugs that increase the risk of hypercalcemia (e.g., calcipotriene, estrogen, lithium, parathyroid hormone, teriparatide, thiazide diuretics, Vitamin A, and Vitamin D).

8 USE IN SPECIFIC POPULATIONS

8.1 Pregnancy

Risk Summary

Administration of Calcium Chloride Injection for the treatment of acute symptomatic hypocalcemia during pregnancy is not expected to cause major birth defects, miscarriage, or adverse maternal or fetal outcomes. There are risks to the mother and the fetus associated with development of hypocalcemia during pregnancy (see Clinical Considerations). Animal reproduction studies have not been conducted with Calcium Chloride Injection.

The estimated background risk of major birth defects and miscarriage for the indicated populations are unknown. All pregnancies have a background risk of birth defect, loss, or other adverse outcomes. In the U.S. general population, the estimated background risk of major birth defects and miscarriage in clinically recognized pregnancies is 2 to 4% and 15 to 20%, respectively.

Clinical Considerations

Disease-associated Maternal and/or Embryo/Fetal/Neonatal Risk

Maternal hypocalcemia can result in an increased rate of spontaneous abortion, premature and dysfunctional labor, and possibly preeclampsia. Infants born to mothers with hypocalcemia can develop fetal and neonatal hyperparathyroidism, which in turn can cause fetal and neonatal skeletal demineralization, subperiosteal bone resorption, osteitis fibrosa cystica and neonatal seizures.

8.2 Lactation

Risk Summary

Calcium is present in human milk. Administration of the approved recommended dose of Calcium Chloride Injection to the mother is not expected to cause harm to a breastfed infant. There is no information on the effects of Calcium Chloride Injection on the breastfed infant or on milk production. The developmental and health benefits of breastfeeding should be considered along with the mother’s clinical need for Calcium Chloride Injection and any potential adverse effects on the breastfed infant from Calcium Chloride Injection or from the underlying maternal condition.

8.4 Pediatric Use

The safety and effectiveness of Calcium Chloride Injection for the treatment of acute symptomatic hypocalcemia have been established in pediatric patients.

The use of Calcium Chloride Injection is contraindicated in newborns if they require (or are expected to require) ceftriaxone intravenous treatment because of the risk of precipitation of ceftriaxone-calcium, regardless of whether these products would be received at different times or through separate intravenous lines [see Contraindications (4) and Warnings and Precautions (5.1)].

In pediatric patients older than 28 days of age, Calcium Chloride Injection and ceftriaxone intravenous solutions may be administered sequentially one after another if infusion lines at different sites are used, infusion lines are replaced, or infusion lines are thoroughly flushed between infusions with physiological salt solution to avoid precipitation. Do not mix or administer Calcium Chloride Injection simultaneously with ceftriaxone, even if using different infusion lines or different infusion sites as it can lead to precipitation of ceftriaxone-calcium.

Calcium Chloride Injection contains aluminum that may be associated with central nervous system and bone toxicity. Because of immature renal function, preterm infants receiving prolonged parenteral nutrition treatment with Calcium Chloride Injection may be at higher risk of aluminum toxicity [see Warnings and Precautions (5.2)].

8.5 Geriatric Use

Clinical studies of Calcium Chloride Injection did not include sufficient numbers of patients 65 years of age and older to determine whether they respond differently from younger adult patients.

8.6 Renal Impairment

The use of Calcium Chloride Injection in patients with renal impairment may increase the risk of a higher calcium-phosphorus product. For patients with renal impairment, initiate Calcium Chloride Injection at the lowest recommended dose within the recommended dose range [see Dosage and Administration (2.2)]. Monitor serum calcium levels frequently based on the severity of the renal impairment and the risk of a high calcium-phosphorus product (e.g., every 4 hours).

10 OVERDOSAGE

Overdosage of Calcium Chloride Injection may lead to hypercalcemia. Symptoms of hypercalcemia typically develop when the total serum calcium concentration is ≥12 mg/dL, and include shortening of QT interval, bradycardia, hypertension, anorexia, nausea, vomiting, bowel hypomotility and constipation, muscle weakness, bone pain, decreased concentration, depression, weakness, fatigue, confusion, hallucinations, disorientation, hypotonicity, seizures, and coma. Hypercalcemia effects on kidney include diminished ability to concentrate urine and diuresis.

In the event of overdosage, promptly discontinue Calcium Chloride Injection , the patient should be re-evaluated and appropriate countermeasures should be instituted, if necessary [see Warnings and Precautions (5), Adverse Reactions (6)].

11 DESCRIPTION

10% Calcium Chloride Injection, USP is a sterile, nonpyrogenic, hypertonic solution for single administration only. Each mL contains 100 mg (1.4 mEq/mL) of calcium chloride, dihydrate (1.4 mEq each of Ca^++ and Cl^-) in water for injection. It is provided in a 10 mL single-dose syringe for intravenous injection. The solution contains no bacteriostat, antimicrobial agent or added buffer. The pH of 10% Calcium Chloride Injection, USP is 5.5 to 7.5 when diluted with water for injection to make a 5% solution. May contain hydrochloric acid and/or sodium hydroxide for pH adjustment. The osmolar concentration is 2.04 mOsmol/mL (calc.). 10% Calcium Chloride Injection, USP is oxygen sensitive.

Calcium Chloride, USP dihydrate is chemically designated CaCl2 • 2H2O (dihydrate) and is described as white, odorless fragments or granules freely soluble in water.

Calcium Chloride Injection, USP contains no more than 1,000 mcg/L of aluminum [see Warnings and Precautions (5.2)].

12 CLINICAL PHARMACOLOGY

12.1 Mechanism of Action

Intravenous administration of calcium chloride increases serum ionized calcium concentration. Calcium chloride dissociates into ionized calcium in plasma.

12.2 Pharmacodynamics

The exposure-response relationship and time course of pharmacodynamic response for the safety and effectiveness of Calcium Chloride Injection have not been fully characterized.

12.3 Pharmacokinetics

Absorption

Calcium Chloride Injection is 100% bioavailable following intravenous injection.

Distribution

Calcium in the body is distributed mainly in skeleton (99%) and 1% is distributed within the extracellular fluids and soft tissues. About 50% of total serum calcium is in the ionized form and represents the biologically active part; 8% to 10% serum calcium is bound to organic and inorganic acid, respectively; and approximately 40% is protein-bound (primarily to albumin).

Elimination

Metabolism

Calcium itself does not undergo direct metabolism.

Excretion

Calcium is excreted by the kidney through a combination of glomerular filtration and tubular reabsorption. A significant increase in urinary excretion of calcium was observed during and after intravenous infusion of calcium chloride.

Specific Populations

The effect of age, sex, race, ethnicity, renal or hepatic impairment on the pharmacokinetics of calcium have not been evaluated in clinical studies.

13 NONCLINICAL TOXICOLOGY

13.1 Carcinogenesis, Mutagenesis, Impairment of Fertility

Carcinogenicity, mutagenicity, and fertility have not been assessed with Calcium Chloride Injection.

16 HOW SUPPLIED/STORAGE AND HANDLING

Calcium Chloride Injection, USP (clear solution) is supplied in single-dose syringes as follows:

Unit of Sale and Product Description | Strength | NDC
Bundle of 10; 10 mL Ansyr® Plastic Syringe | 10% (1,000 mg/10 mL); (100 mg/mL) | 0409-1631-10

The 100 mg/mL concentration represents 27 mg or 1.4 mEq of elemental calcium per mL of solution.

Store at 20°C to 25°C (68°F to 77°F); excursions permitted between 15°C and 30°C (59°F and 86°F). [See USP Controlled Room Temperature.]

17 PATIENT COUNSELING INFORMATION

Inform patients or caregivers of the following risks of Calcium Chloride Injection:

Arrhythmias with Concomitant Digoxin Use

Arrhythmias may occur if Calcium Chloride Injection and Digoxin are administered together [see Warnings and Precautions (5.3)].

Tissue Necrosis and Calcinosis

Administration of Calcium Chloride Injection may result in calcinosis cutis including tissue necrosis, ulceration, and secondary infection. [see Warnings and Precautions (5.4)].

Aluminum Toxicity

Calcium Chloride Injection contains aluminum that may be toxic [see Warnings and Precautions (5.5)].

Distributed by Hospira, Inc., Lake Forest, IL 60045 USA

LAB-1022-4.0

PACKAGE/LABEL PRINCIPAL DISPLAY PANEL

10 mL Single-Dose Syringe - Discard Unused Portion NDC 0409-1631-40

10% Calcium Chloride Injection, USP
1000 mg/10 mL (100 mg/mL)

For Intravenous use only.
2.04 mOsmol/mL (calc.). pH (5.5 to 7.5). Contains no more than 1,000 mcg/L
of aluminum.

Hospira

Distributed by Hospira, Inc., Lake Forest, IL 60045 USA
Rx only

RL-7161

PRINCIPAL DISPLAY PANEL - 10 mL Syringe Carton

10 mL

NDC 0409-1631-40
Rx only

10%
Calcium
Chloride
Injection, USP

1,000 mg/10 mL
(100 mg/mL)

For Intravenous use only

Ansyr®

Single-Dose Syringe
Discard Unused Portion

Hospira

LOT #####AA
EXP DMMMYYYY

◀ PRESS AND PULL TO OPEN ▶